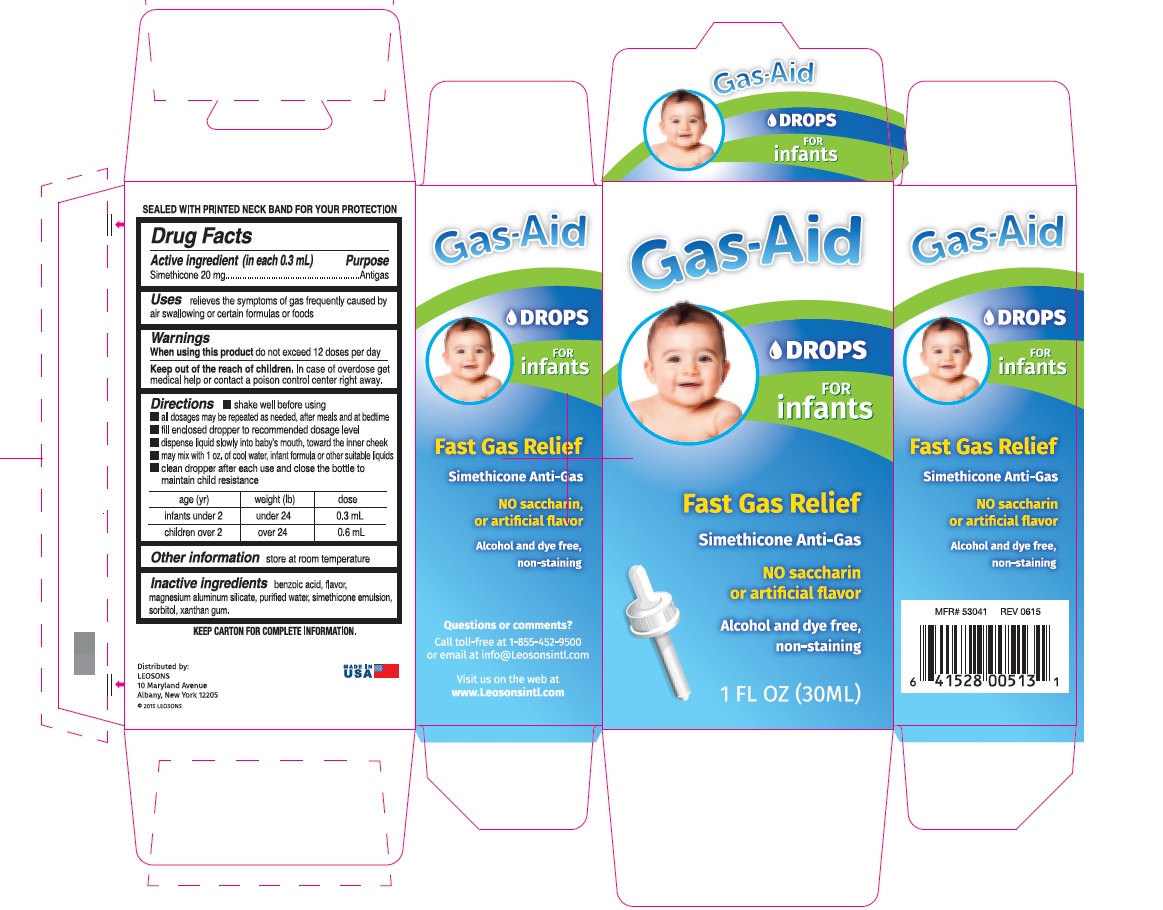 DRUG LABEL: Gas-Aid Drops for infants
NDC: 69626-5200 | Form: EMULSION
Manufacturer: Leosons Overseas Corp
Category: otc | Type: HUMAN OTC DRUG LABEL
Date: 20241119

ACTIVE INGREDIENTS: DIMETHICONE 20 mg/0.3 mL
INACTIVE INGREDIENTS: BENZOIC ACID; MAGNESIUM ALUMINUM SILICATE; WATER; SORBITOL; XANTHAN GUM

Gas-Aid Drops for Infant's

Active ingredient (in each 0.3 mL)

simethicone 20 mg

Purpose

Antigas

Uses

relieves the symptoms of gas frequently caused by air swallowing or certain formulas or foods

Warnings

When using this product

do not exceed 12 doses per day

Keep out of reach of children. In case of overdose get medical help or contact a poison control center immediately.

Directions

- shake well before using
- all dosages may be repeated as needed, after meals and at bedtime
- fill enclosed dropper to recommend dosage level
- dispense liquid slowly into baby's mouth, toward the inner cheek
- may mix with 1 oz. of cool water, infant formula or other suitable liquids
- clean dropper after each use and close the bottle to maintain child resistance

age (yr) | weight (lb) | dose
infants under2 | under 24 | 0.3 mL
children over 2 | over 24 | 0.6 mL

Other information

store at room temperature

Inactive ingredients

benzoic acid, flavor, magnesium aluminum silicate, purified water, simethicone emulsion, sorbitol, xanthan gum

Principal Display Panel

Gas-Aid drops for infant's

Fast relief of

Simethicone Anti-Gas

No Saccharin or artificial flavor

Alcohol and dye Free

Non-staining

1 fl oz (30 mL)